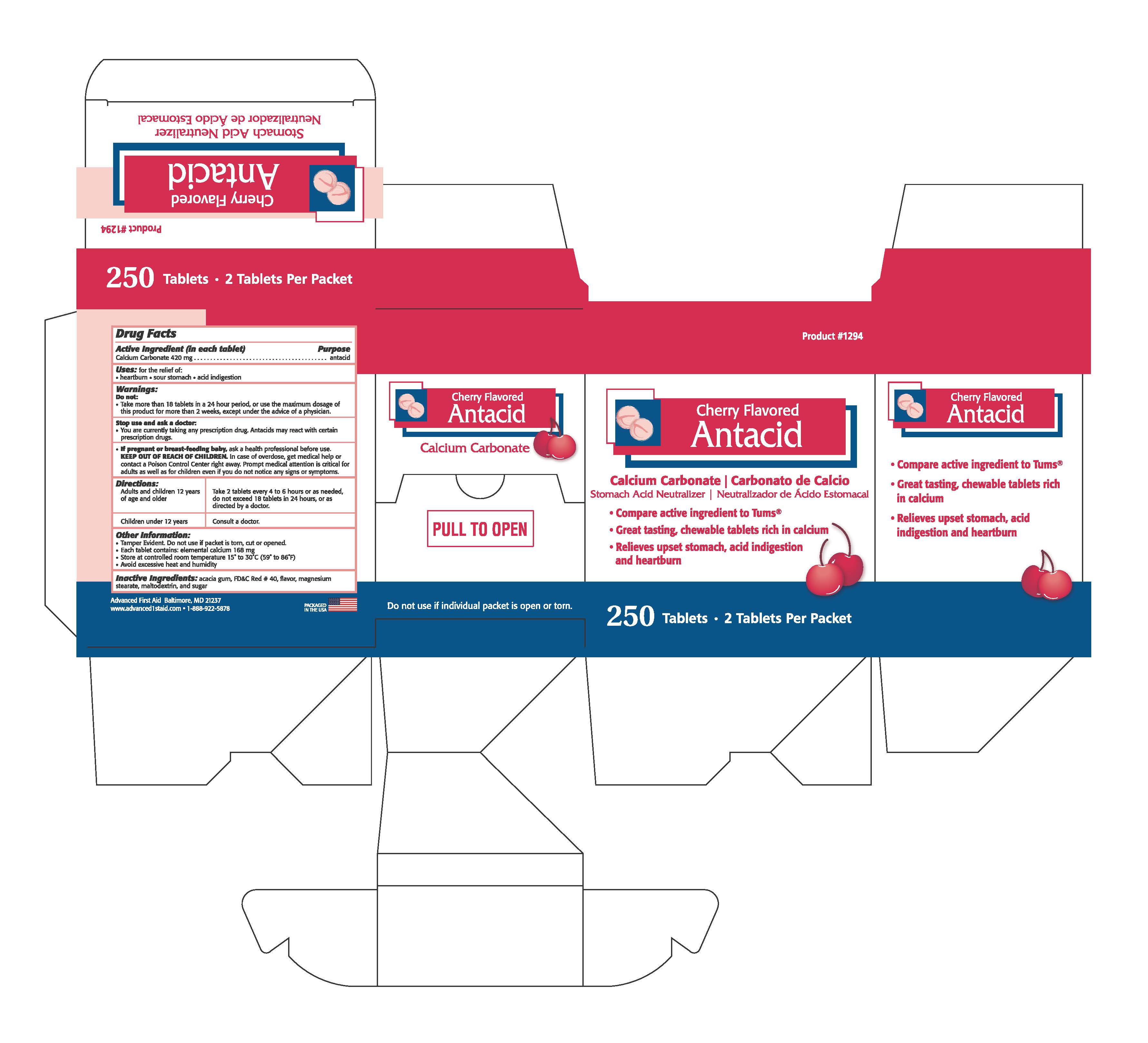 DRUG LABEL: CHERRY ANTACID
NDC: 67060-304 | Form: TABLET, CHEWABLE
Manufacturer: ADVANCED FIRST AID, INC.
Category: otc | Type: HUMAN OTC DRUG LABEL
Date: 20190313

ACTIVE INGREDIENTS: CALCIUM CARBONATE 420 1/1 1
INACTIVE INGREDIENTS: FD&C RED NO. 40; SUCROSE; MAGNESIUM STEARATE; ACACIA; MALTODEXTRIN

ACTIVE INGREDIENT IN EACH TABLET- CALCIUM CARBONATE 420 MG

PURPOSE

ANTACID

Uses:

for the relief of:

•heartburn • sour stomach • acid indigestion

Warnings:

Do not:

•Take more than 18 tablets in a 24 hour period, or use the maximum dosage of

this product for more than 2 weeks, except under the advice of a physician.

Stop use and ask a doctor if:

•You are currently taking any prescription drug. Antacids may react with certain

prescription drugs.

If pregnant or breast-feeding baby,

ask a health professional before use.

KEEP OUT OF REACH OF CHILDREN.

In case of overdose, get medical help or

contact a Poison Control Center right away. Prompt medical attention is critical for

adults as well as for children even if you do not notice any signs or symptoms.

Directions:

Adults and children 12 years of age and older: Take 2 tablets every 4 to

6 hours or as needed, do not exceed 18 tablets

in 24 hours, or asdirected by a doctor.

Children under 12 years: Consult a doctor.

INACTIVE INGREDIENT

Inactive Ingredients: acacia gum, FD&C Red #40, flavor, magnesium stearate, maltodextrin, and sugar.